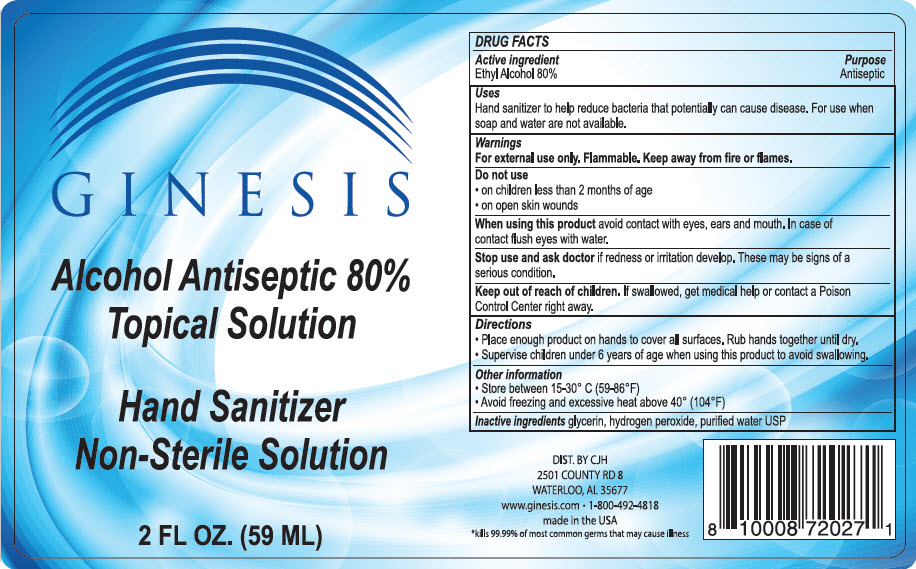 DRUG LABEL: Hand Sanitizer
NDC: 79703-080 | Form: LIQUID
Manufacturer: Ginesis Natural Products
Category: otc | Type: HUMAN OTC DRUG LABEL
Date: 20200827

ACTIVE INGREDIENTS: Alcohol 80 mL/100 mL
INACTIVE INGREDIENTS: glycerin; hydrogen peroxide; water

Hand Sanitizer

DRUG FACTS

Active ingredient

Ethyl Alcohol 80%

Purpose

Antiseptic

Uses

Hand sanitizer to help reduce bacteria that potentially can cause disease. For use when soap and water are not available.

Warnings

For external use only. Flammable. Keep away from fire or flames.

Do not use

- on children less than 2 months of age
- on open skin wounds

When using this product avoid contact with eyes, ears and mouth. In case of contact flush eyes with water.

Stop use and ask doctor if redness or irritation develop. These may be signs of a serious condition.

Keep out of reach of children. If swallowed, get medical help or contact a Poison Control Center right away.

Directions

- Place enough product on hands to cover all surfaces. Rub hands together until dry.
- Supervise children under 6 years of age when using this product to avoid swallowing.

Other information

- Store between 15-30° C (59-86°F)
- Avoid freezing and excessive heat above 40° (104°F)

Inactive ingredients

glycerin, hydrogen peroxide, purified water USP

DIST. BY CJH
2501 COUNTY RD 8
WATERLOO, AL 35677

PRINCIPAL DISPLAY PANEL - 59 ML Bottle Label

GINESIS

Alcohol Antiseptic 80%
Topical Solution

Hand Sanitizer
Non-Sterile Solution

2 FL OZ. (59 ML)